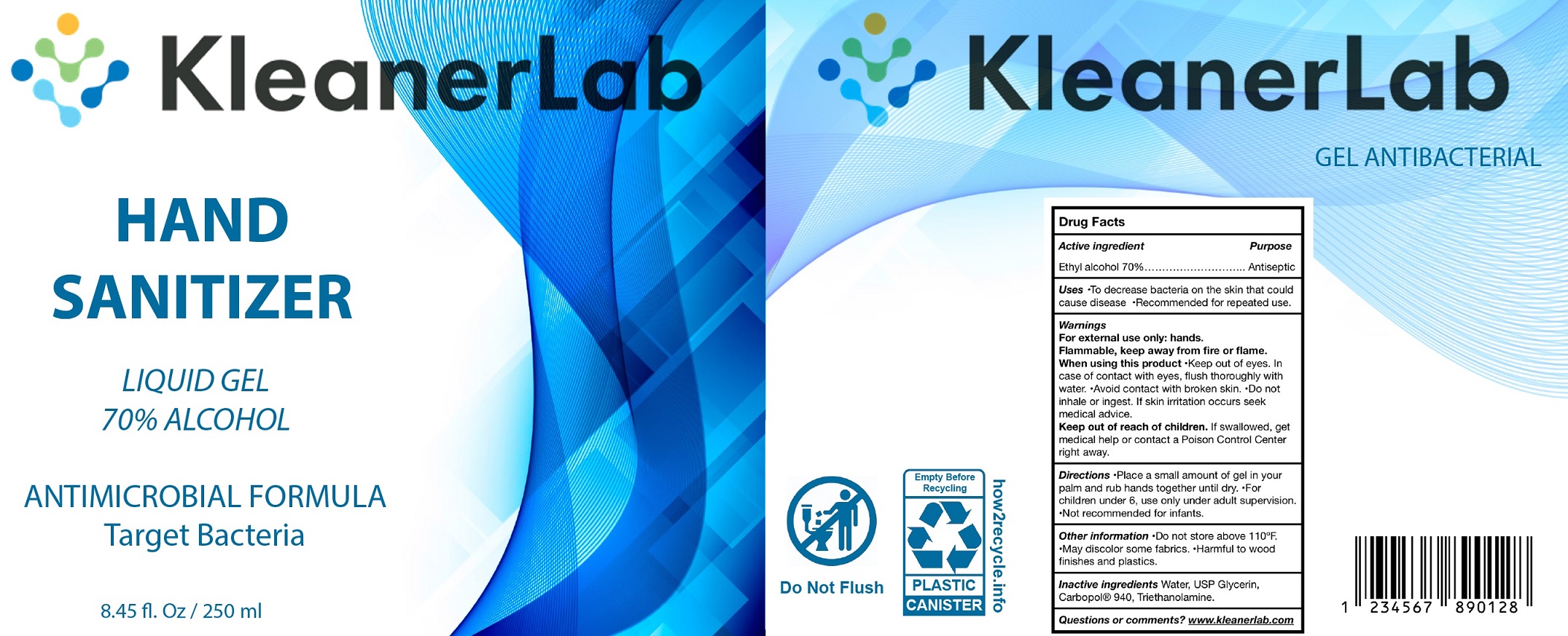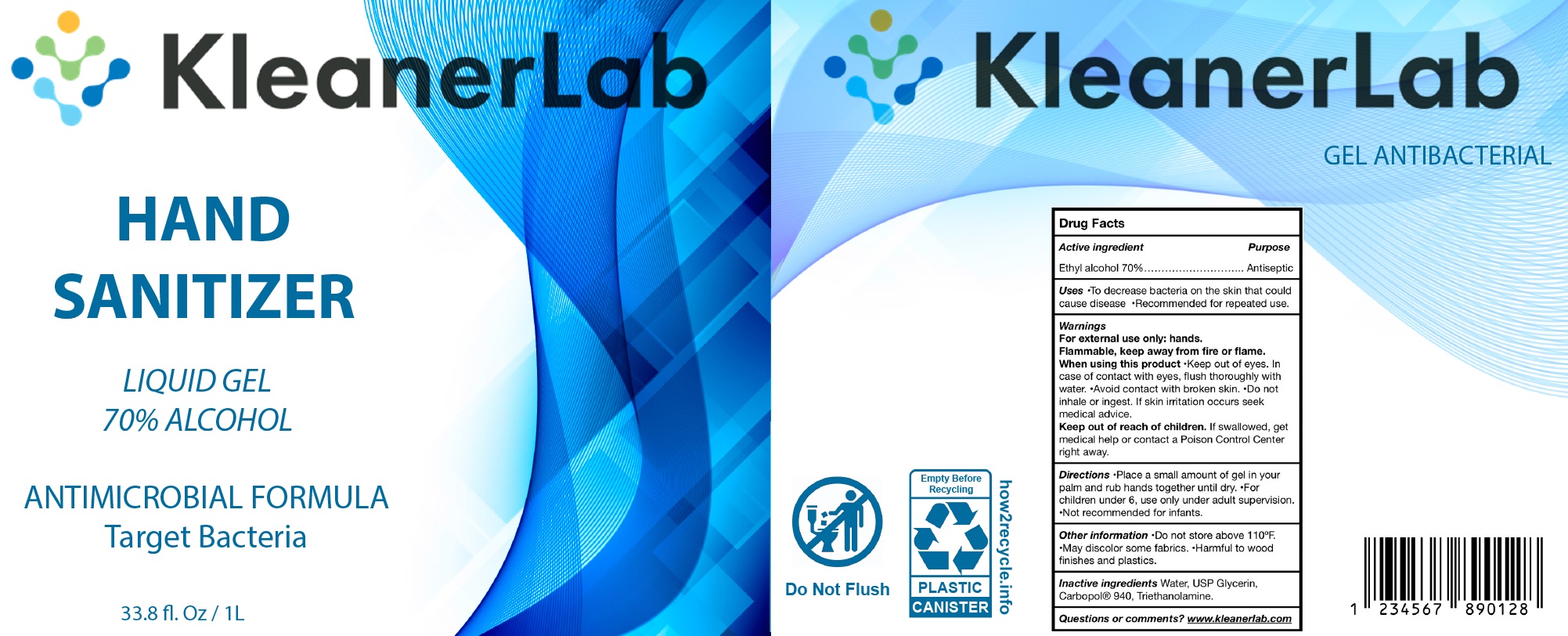 DRUG LABEL: Kleanerlab Hand Sanitizer
NDC: 80226-000 | Form: GEL
Manufacturer: Laboratorios Elizondo S.A. de C.V.
Category: otc | Type: HUMAN OTC DRUG LABEL
Date: 20200929

ACTIVE INGREDIENTS: ALCOHOL 0.7 mL/1 mL
INACTIVE INGREDIENTS: WATER; GLYCERIN; CARBOMER HOMOPOLYMER TYPE C (ALLYL PENTAERYTHRITOL CROSSLINKED); TROLAMINE

Kleanerlab Hand Sanitizer

Active ingredient

Ethyl alcohol 70%

Purpose

Antiseptic

Uses

- To decrease bacteria on the skin that could cause disease
- Recommended for repeated use.

Warnings

For external use only: hands.

Flammable, keep away from fire or flame.

When using this product

- Keep out of eyes. In case of contact with eyes, flush thoroughly with water.
- Avoid contact with broken skin.
- Do not inhale or ingest. If skin irritation occurs seek medical advice.

Keep out of reach of children.

If swallowed, get medical help or contact a Poison Control Center right away.

Directions

- Place a small amount of gel in your palm and rub hands together until dry.
- For children under 6, use only under adult supervision.
- Not recommended for infants

Other information

- Do not store above 110°F.
- May discolor some fabrics.
- Harmful to wood finishes and plastics.

Inactive ingredients

Water, USP Glycerin, Carbopol 940, Triethanolamine.

Questions or comments?

www.kleanerlab.com